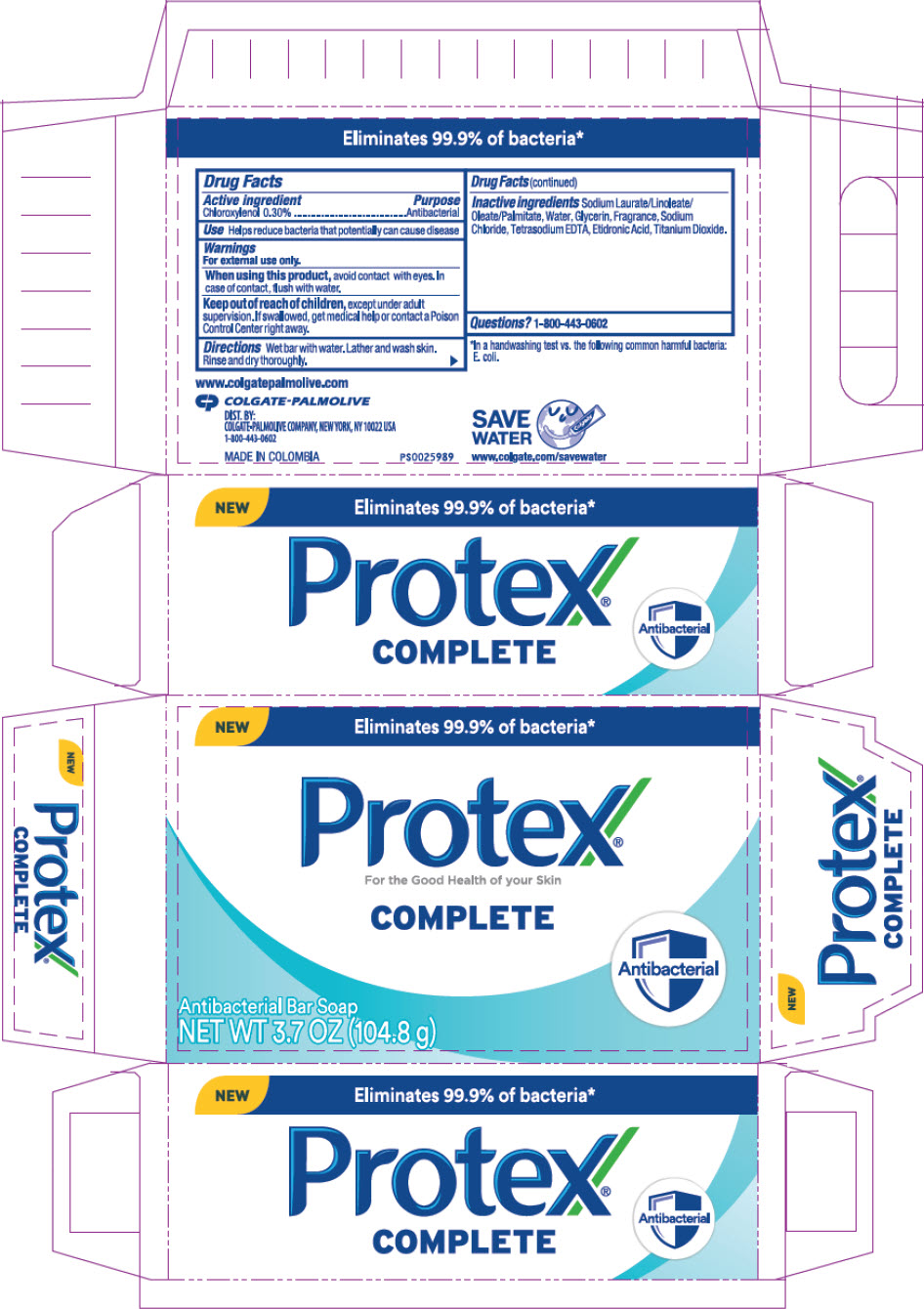 DRUG LABEL: Protex Complete Antibacterial Bar
NDC: 35000-069 | Form: SOAP
Manufacturer: Colgate-Palmolive Company
Category: otc | Type: HUMAN OTC DRUG LABEL
Date: 20260123

ACTIVE INGREDIENTS: CHLOROXYLENOL 3 mg/1 g
INACTIVE INGREDIENTS: SODIUM LAURATE; SODIUM LINOLEATE; SODIUM OLEATE; SODIUM PALMITATE; WATER; GLYCERIN; SODIUM CHLORIDE; EDETATE SODIUM; ETIDRONIC ACID; TITANIUM DIOXIDE

Protex® Complete Antibacterial Bar

Drug Facts

Active ingredient

Chloroxylenol 0.30%

Purpose

Antibacterial

Use

Helps reduce bacteria that potentially can cause disease

Warnings

For external use only.

When using this product, avoid contact with eyes. In case of contact, flush with water.

Keep out of reach of children, except under adult supervision. If swallowed, get medical help or contact a Poison Control Center right away.

Directions

Wet bar with water. Lather and wash skin. Rinse and dry thoroughly.

Inactive ingredients

Sodium Laurate/Linoleate/Oleate/Palmitate, Water, Glycerin, Fragrance, Sodium Chloride, Tetrasodium EDTA, Etidronic Acid, Titanium Dioxide.

Questions?

1-800-443-0602

DIST. BY:
COLGATE-PALMOLIVE COMPANY, NEW YORK, NY 10022 USA

PRINCIPAL DISPLAY PANEL - 104.8 g Applicator Carton

NEW
Eliminates 99.9% of bacteria*

Protex®
For the Good Health of your Skin
COMPLETE

Antibacterial

Antibacterial Bar Soap
NET WT 3.7 OZ (104.8 g)